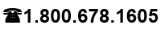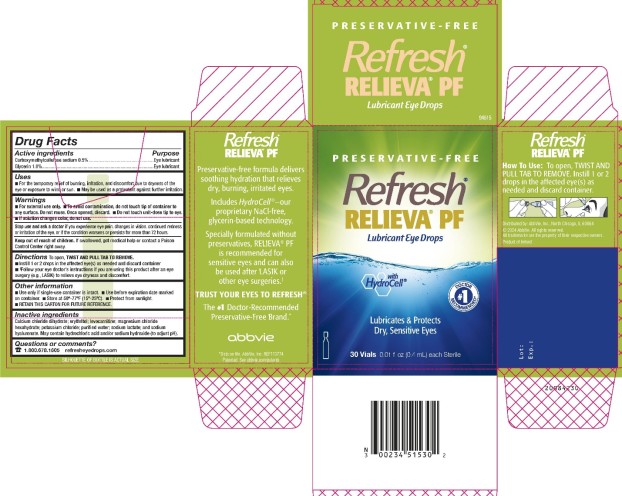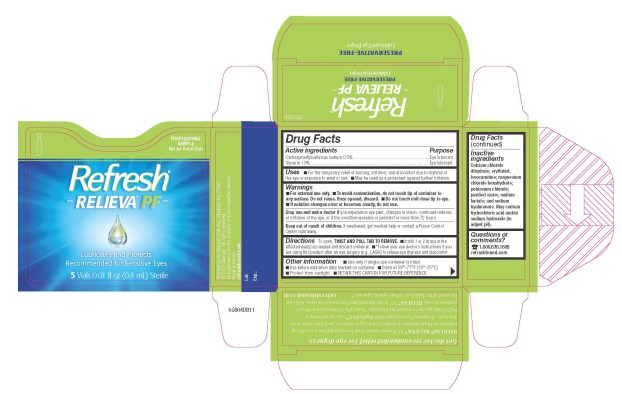 DRUG LABEL: Refresh RELIEVA PF
NDC: 0023-4515 | Form: SOLUTION/ DROPS
Manufacturer: Allergan, Inc.
Category: otc | Type: HUMAN OTC DRUG LABEL
Date: 20250822

ACTIVE INGREDIENTS: CARBOXYMETHYLCELLULOSE SODIUM 5 mg/1 mL; GLYCERIN 10 mg/1 mL
INACTIVE INGREDIENTS: CALCIUM CHLORIDE; ERYTHRITOL; LEVOCARNITINE; MAGNESIUM CHLORIDE; POTASSIUM CHLORIDE; WATER; SODIUM LACTATE; HYALURONATE SODIUM; HYDROCHLORIC ACID; SODIUM HYDROXIDE

REFRESH® RELIEVA® PF
Drug Facts

Active ingredients

Carboxymethylcellulose sodium 0.5%

Glycerin 1.0%

Purpose

Eye lubricant

Eye lubricant

Uses

- For the temporary relief of burning, irritation, and discomfort due to dryness of the eye or exposure to wind or sun.
- May be used as a protectant against further irritation.

Warnings

- For external use only.
- To avoid contamination, do not touch tip of container to any surface. Do not reuse. Once opened, discard.
- Do not touch unit-dose tip to eye.
- If solution changes color or becomes cloudy, do not use.

Stop use and ask a doctor if

you experience eye pain, changes in vision, continued redness or irritation of the eye, or if the condition worsens or persists for more than 72 hours.

Keep out of reach of children.

If swallowed, get medical help or contact a Poison Control Center right away.

Directions

To open, TWIST AND PULL TAB TO REMOVE.

- Instill 1 or 2 drops in the affected eye(s) as needed and discard container
- *Follow your eye doctor’s instructions if you are using this product after an eye surgery (e.g., LASIK) to relieve eye dryness and discomfort.

Other information

- Use only if single-use container is intact.
- Use before expiration date marked on container.
- Store at 59°-77°F (15°-25°C).
- Protect from sunlight.
- RETAIN THIS CARTON FOR FUTURE REFERENCE.

Inactive ingredients

Calcium chloride dihydrate; erythritol; levocarnitine; magnesium chloride hexahydrate; potassium chloride; purified water; sodium lactate; and sodium hyaluronate. May contain hydrochloric acid and/or sodium hydroxide (to adjust pH).

Questions or comments?

refresheyedrops.com

v2.0DFL4515

PRINCIPAL DISPLAY PANEL

NDC 0023 4515 30
PRESERVATIVE-FREE
Refresh®
RELIEVA® PF
Lubricant Eye Drops
With HydroCell®
Lubricates & Protects
Dry, Sensitive Eyes
30 Vials 0.01 fl oz (0.4 mL) each Sterile

PRINCIPAL DISPLAY PANEL

NDC 0023 9537 05
Refresh®
RELIEVA™ PF
Lubricates and Protects
Recommended for Sensitive Eyes
5 Vials 0.01 fl oz (0.4 mL) Sterile